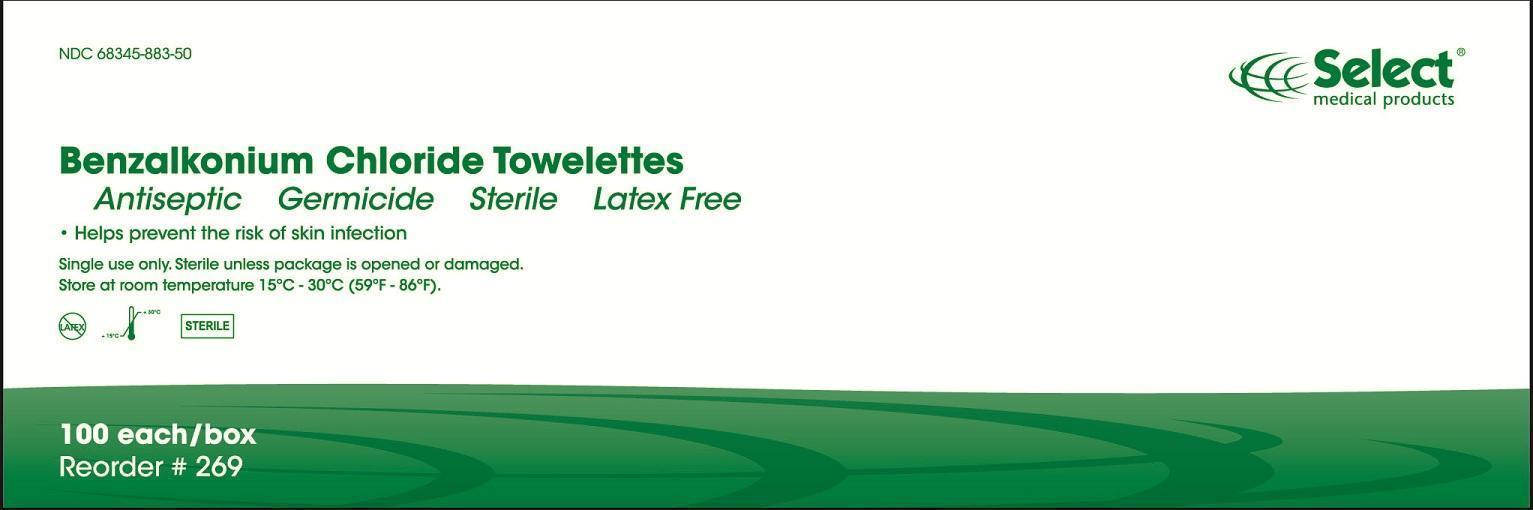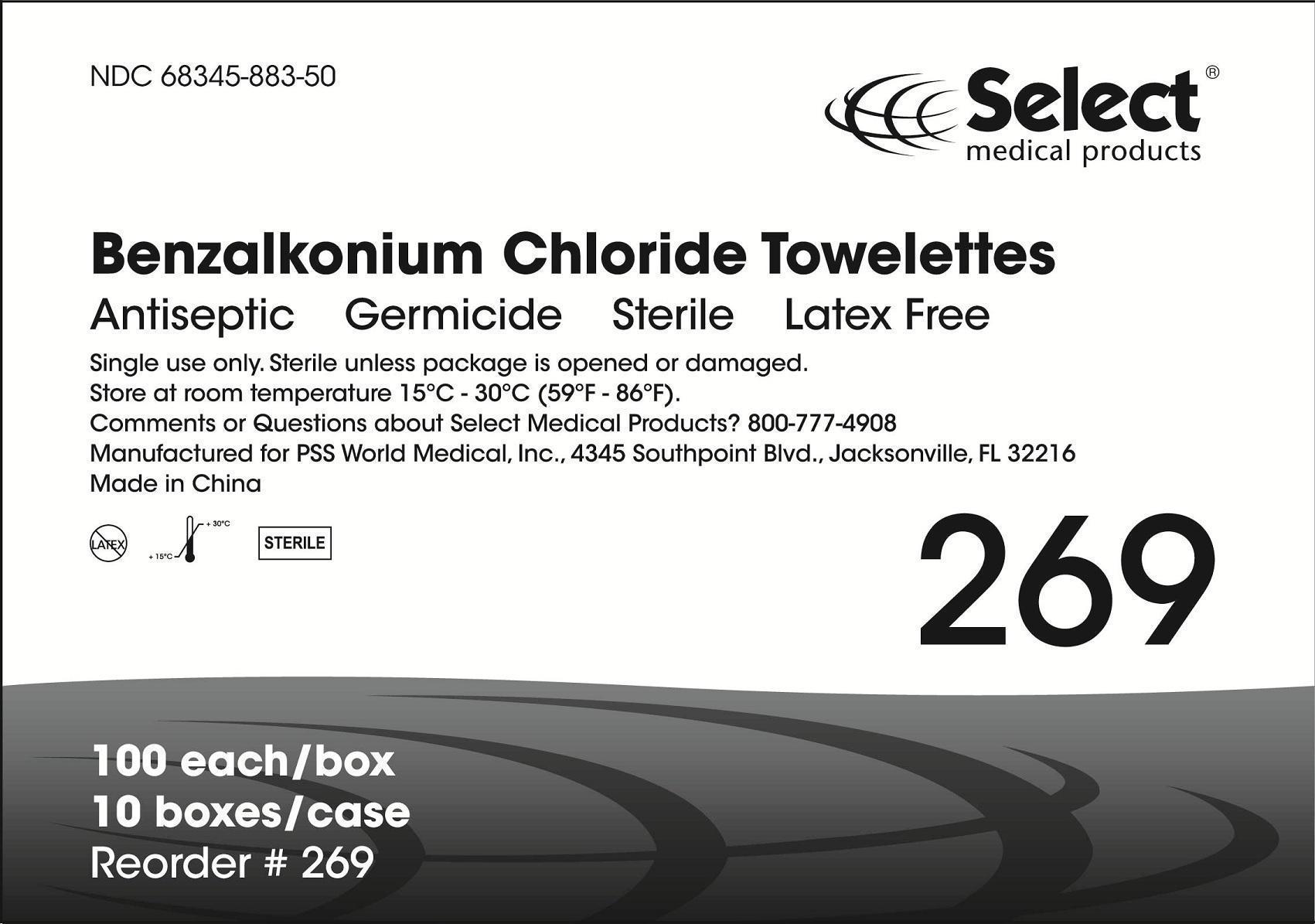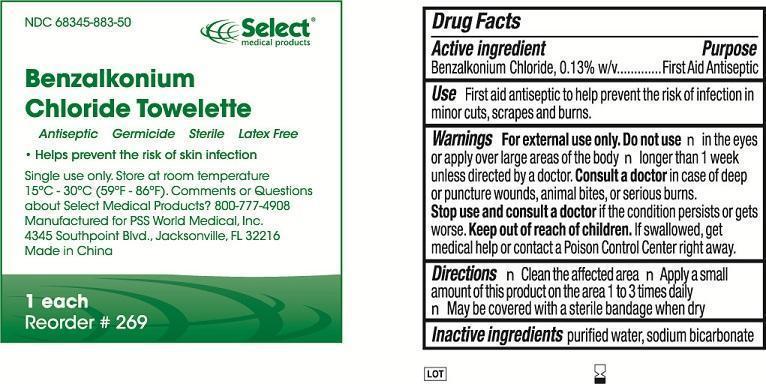 DRUG LABEL: Benzalkonium Chloride Towelette
NDC: 68345-883 | Form: LIQUID
Manufacturer: PSS World Medical, Inc.
Category: otc | Type: HUMAN OTC DRUG LABEL
Date: 20130627

ACTIVE INGREDIENTS: BENZALKONIUM CHLORIDE 0.13 g/100 g
INACTIVE INGREDIENTS: WATER; SODIUM BICARBONATE

BENZALKONIUM CHLORIDE TOWELETTE (benzalkonium chloride) liquid
[PSS World Medical]

Active ingredient

Benzalkonium Chloride, 0.13% w/v

Purpose

First Aid Antiseptic

INDICATIONS AND USAGE

Use First aid antiseptic to help prevent the risk of infection in minor cuts, scrapes and burns.

Warnings

For external use only.

Do not use

- in the eyes or apply over large areas of the body.
- longer than 1 week unless directed by a doctor.

STOP USE

Consult a doctor in case of deep or puncture wounds, animal bites, or serious burns.

Stop use and consult a doctor if the condition persists or gets worse.

Keep out of reach of children. If swallowed, get medical help or contact a Poison Control Center right away.

Directions

- Clean the affected area
- Apply a small amount of this product on the area 1 to 3 times daily
- May be covered with a sterile bandage when dry

Inactive ingredients purified water, sodium bicarbonate

QUESTIONS

Comments or Questions about Select Medical Products? 800-777-4908

DESCRIPTION

Manufactured for PSS World Medical, Inc.

4345 Southpoint Blvd., Jacksonville, FL 32216

Made in China www.myselectonline.com

Package Label

Reorder #269

NDC 68345-883-50

269_Each

269_Box

269_Case